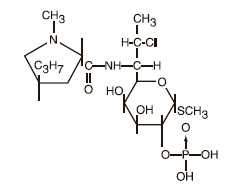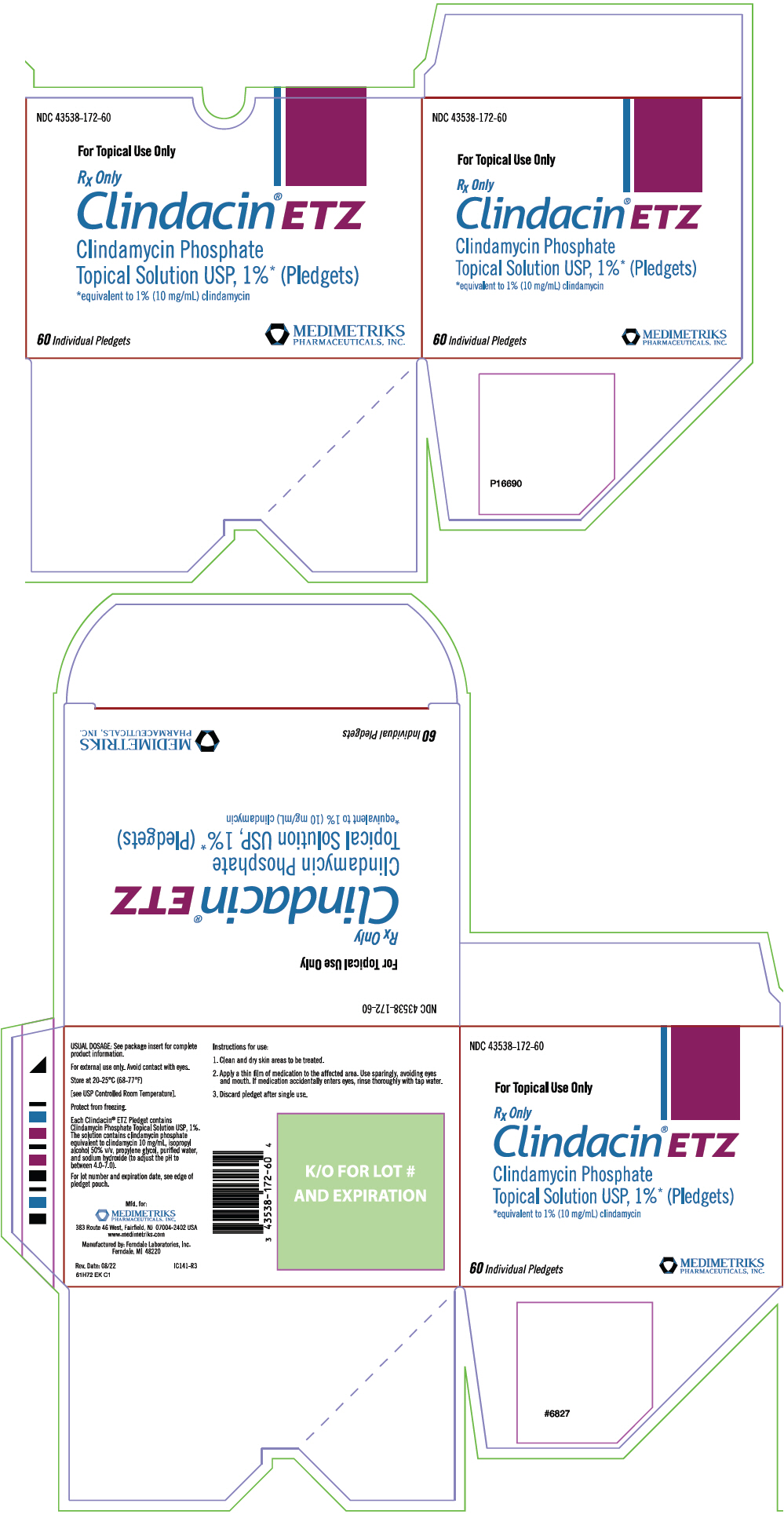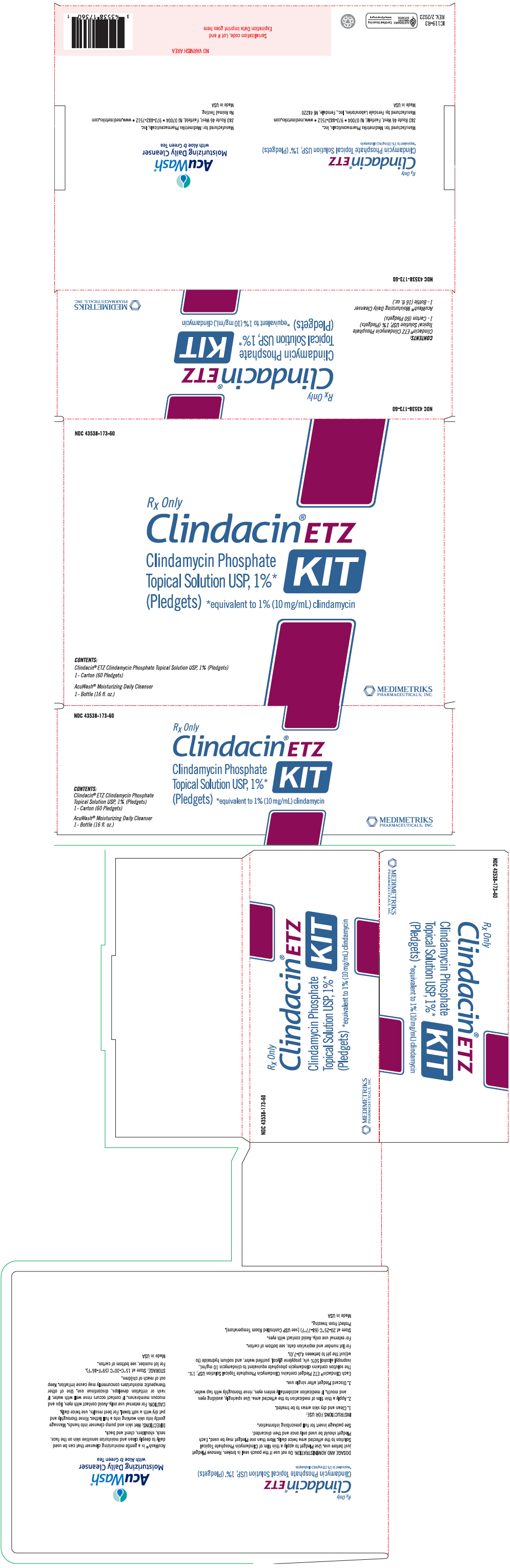 DRUG LABEL: Clindacin ETZ
NDC: 43538-172 | Form: SWAB
Manufacturer: Medimetriks Pharmaceuticals, Inc.
Category: prescription | Type: HUMAN PRESCRIPTION DRUG LABEL
Date: 20241212

ACTIVE INGREDIENTS: clindamycin phosphate 10 mg/1 1
INACTIVE INGREDIENTS: isopropyl alcohol; propylene glycol; water; sodium hydroxide

Clindacin® ETZ
Clindamycin Phosphate Topical Solution
USP, 1% (Pledgets)

Rx Only

For External Use

DESCRIPTION

Clindacin® ETZ contains clindamycin phosphate, USP, at a concentration equivalent to 10 mg clindamycin per milliliter.

Each Clindacin® ETZ pledget applicator contains approximately 1 mL of topical solution.

Clindamycin phosphate is a water soluble ester of the semi-synthetic antibiotic produced by a 7(S)-chloro-substitution of the 7(R)-hydroxyl group of the parent antibiotic lincomycin.

The solution contains isopropyl alcohol 50% v/v, propylene glycol, purified water, and sodium hydroxide (to adjust the pH to between 4.0 - 7.0).

The structural formula is represented below:

The chemical name for clindamycin phosphate is Methyl 7-chloro-6,7,8-trideoxy-6-(1-methyl-trans-4-propyl-L-2-pyrrolidinecarboxamido)-1-thio-L-threo-α-D-galacto-octopyranoside 2-(dihydrogen phosphate).

CLINICAL PHARMACOLOGY

Although clindamycin phosphate is inactive in vitro, rapid in vivo hydrolysis converts this compound to the antibacterially active clindamycin.

Cross resistance has been demonstrated between clindamycin and lincomycin. Antagonism has been demonstrated between clindamycin and erythromycin.

Following multiple topical applications of clindamycin phosphate at a concentration equivalent to 10 mg clindamycin per mL in an isopropyl alcohol and water solution, very low levels of clindamycin are present in the serum (0-3 ng/mL) and less than 0.2% of the dose is recovered in urine as clindamycin.

Clindamycin activity has been demonstrated in comedones from acne patients. The mean concentration of antibiotic activity in extracted comedones after application of clindamycin phosphate topical solution for 4 weeks was 597 mcg/g of comedonal material (range 0-1490). Clindamycin in vitro inhibits all Propionibacterium acnes cultures tested (MICs 0.4 mcg/mL). Free fatty acids on the skin surface have been decreased from approximately 14% to 2% following application of clindamycin.

INDICATIONS AND USAGE

Clindacin® ETZ is indicated in the treatment of acne vulgaris. In view of the potential for diarrhea, bloody diarrhea and pseudomembranous colitis, the physician should consider whether other agents are more appropriate (see CONTRAINDICATIONS, WARNINGS and ADVERSE REACTIONS).

CONTRAINDICATIONS

Clindacin® ETZ is contraindicated in individuals with a history of hypersensitivity to preparations containing clindamycin or lincomycin, a history of regional enteritis or ulcerative colitis, or a history of antibiotic-associated colitis.

WARNINGS

Orally and parenterally administered clindamycin has been associated with severe colitis which may result in patient death. Use of the topical formulation of clindamycin results in absorption of the antibiotic from the skin surface. Diarrhea, bloody diarrhea, and colitis (including pseudomembranous colitis) have been reported with the use of topical and systemic clindamycin.

Studies indicate a toxin(s) produced by clostridia is one primary cause of antibiotic-associated colitis. The colitis is usually characterized by severe persistent diarrhea and severe abdominal cramps and may be associated with the passage of blood and mucus. Endoscopic examination may reveal pseudomembranous colitis. Stool culture for Clostridium difficile and stool assay for C. difficile toxin may be helpful diagnostically.

When significant diarrhea occurs, the drug should be discontinued. Large bowel endoscopy should be considered to establish a definitive diagnosis in cases of severe diarrhea.

Antiperistaltic agents such as opiates and diphenoxylate with atropine may prolong and/or worsen the condition. Vancomycin has been found to be effective in the treatment of antibiotic-associated pseudomembranous colitis produced by Clostridium difficile. The usual adult dosage is 500 milligrams to 2 grams of vancomycin orally per day in three to four divided doses administered for 7 to 10 days. Cholestyramine or colestipol resins bind vancomycin in vitro. If both a resin and vancomycin are to be administered concurrently, it may be advisable to separate the time of administration of each drug.

Diarrhea, colitis, and pseudomembranous colitis have been observed to begin up to several weeks following cessation of oral and parenteral therapy with clindamycin.

PRECAUTIONS

General

Clindacin® ETZ contains an alcohol base which will cause burning and irritation of the eye. In the event of accidental contact with sensitive surfaces (eye, abraded skin, mucous membranes), bathe with copious amounts of cool tap water. The solution has an unpleasant taste and caution should be exercised when applying medication around the mouth. Clindamycin phosphate topical products should be prescribed with caution in atopic individuals.

Drug Interactions

Clindamycin has been shown to have neuromuscular blocking properties that may enhance the action of other neuromuscular blocking agents. Therefore it should be used with caution in patients receiving such agents.

Pregnancy

Teratogenic Effects

Pregnancy Category B

In clinical trials with pregnant women, the systemic administration of clindamycin during the second and third trimesters has not been associated with an increased frequency of congenital abnormalities. There are no adequate studies in pregnant women during the first trimester of pregnancy. Clindamycin should be used during the first trimester of pregnancy only if clearly needed.

Nursing Mothers

It is not known whether clindamycin is excreted in human milk following use of Clindacin® ETZ. However, orally and parenterally administered clindamycin has been reported to appear in breast milk. Because of the potential for serious adverse reactions in nursing infants, a decision should be made whether to discontinue nursing or to discontinue the drug, taking into account the importance of the drug to the mother.

Pediatric Use

Safety and effectiveness in pediatric patients under the age of 12 have not been established.

Geriatric Use

Clinical studies for clindamycin phosphate topical solution USP, 1% did not include sufficient numbers of subjects aged 65 and over to determine whether they respond differently from younger subjects. Other reported clinical experience has not identified differences in responses between the elderly and younger patients.

ADVERSE REACTIONS

In 18 clinical studies of various formulations of topical clindamycin phosphate using placebo vehicle and/or active comparator drugs as controls, patients experienced a number of treatment emergent adverse dermatologic events [see table below].

 | Number of Patients Reporting Events
Treatment Emergent Adverse Event | Solution n=553 (%) | Gel n=148 (%) | Lotion n=160 (%)
Burning | 62 (11) | 15 (10) | 17 (11)
Itching | 36 (7) | 15 (10) | 17 (11)
Burning/Itching | 60 (11) | [not recorded] (-) | (-)
Dryness | 105 (19) | 34 (23) | 29 (18)
Erythema | 86 (16) | 10 (7) | 22 (14)
Oiliness/Oily Skin | 8 (1) | 26 (18) | 12 [of 126 subjects] (10)
Peeling | 61 (11) | (-) | 11 (7)

Orally and parenterally administered clindamycin has been associated with severe colitis which may end fatally. Cases of diarrhea, bloody diarrhea and colitis (including pseudomembranous colitis) have been reported as adverse reactions in patients treated with oral and parenteral formulations of clindamycin and rarely with topical clindamycin (see WARNINGS).

Abdominal pain, gastrointestinal disturbances, gram-negative folliculitis, eye pain and contact dermatitis have also been reported in association with the use of topical formulations of clindamycin.

To report SUSPECTED ADVERSE REACTIONS, contact Medimetriks Pharmaceuticals, Inc., at 1-973-882-7512 or FDA at 1-800-FDA-1088 or www.fda.gov/medwatch.

OVERDOSAGE

Topically applied Clindacin® ETZ can be absorbed in sufficient amounts to produce systemic effects (see WARNINGS).

DOSAGE AND ADMINISTRATION

Do not use if the unit-dose pouch seal is broken. Remove pledget just before use. Use pledget to apply a thin film of Clindamycin Phosphate Topical Solution to the affected area twice daily. More than one pledget may be used. Each pledget should be used only once and then discarded.

HOW SUPPLIED

Clindacin® ETZ (Clindamycin Phosphate Topical Solution USP, 1% (Pledgets)) is available as follows:

A carton containing 60 individually wrapped single-use pledget applicators (NDC 43538-172-60)

STORAGE

Store at 20-25°C (68-77°F) [see USP Controlled Room Temperature]. Protect from freezing.

Manufactured by: Ferndale Laboratories, Ferndale, MI 48220

Rev 09/22
IP032-R4
61H72 EK J1

PRINCIPAL DISPLAY PANEL - 60 Pledget Carton

NDC 43538-172-60

For Topical Use Only

Rx Only

Clindacin® ETZ
Clindamycin Phosphate
Topical Solution USP, 1%* (Pledgets)
*equivalent to 1% (10 mg/mL) clindamycin

60 Individual Pledgets

MEDIMETRIKS
PHARMACEUTICALS, INC.

PRINCIPAL DISPLAY PANEL - Kit Carton

NDC 43538-173-60

Rx Only

Clindacin® ETZ
KIT

Clindamycin Phosphate
Topical Solution USP, 1%*
(Pledgets)
*equivalent to 1% (10 mg/mL) clindamycin

CONTENTS:
Clindacin® ETZ Clindamycin Phosphate Topical Solution USP, 1% (Pledgets)
1 - Carton (60 Pledgets)

AcuWash® Moisturizing Daily Cleanser
1 - Bottle (16 fl. oz.)

MEDIMETRIKS
PHARMACEUTICALS, INC.